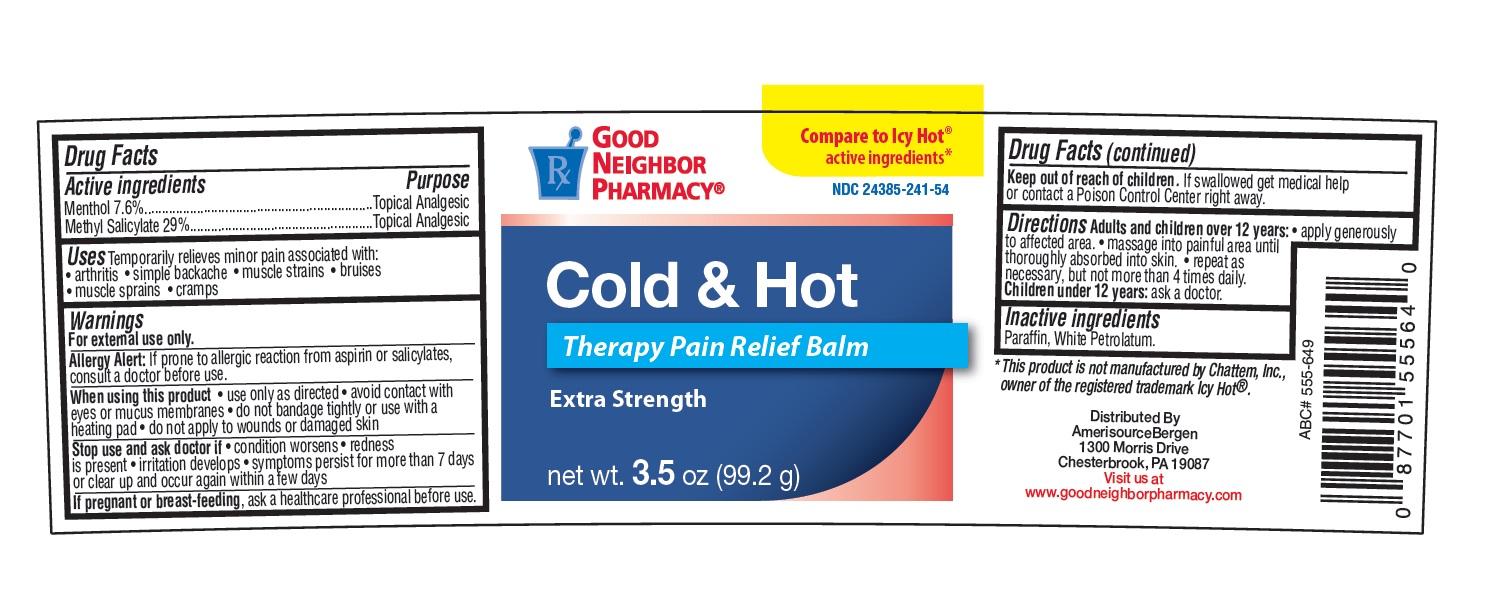 DRUG LABEL: Good Neighbor Pharmacy Cold and Hot Therapy Pain Relief Balm
NDC: 24385-241 | Form: OINTMENT
Manufacturer: AmerisourceBergen Drug Corporation
Category: otc | Type: HUMAN OTC DRUG LABEL
Date: 20150714

ACTIVE INGREDIENTS: MENTHOL 7.6 g/100 g; METHYL SALICYLATE 29 g/100 g
INACTIVE INGREDIENTS: PARAFFIN; PETROLATUM

Good Neighbor Pharmacy Cold and Hot Therapy Pain Relief Balm

Active ingredients

Menthol 7.6%

Methyl Salicylate 29%

Purpose

Topical Analgesic

Uses

Temporarily relieves minor pain associated with:

• arthritis • simple backache • muscle strains • bruises

• muscle sprains • cramps

Warnings

For external use only.

Allergy Alert:

If prone to allergic reaction from aspirin or salicylates, consult a doctor before use.

When using this product

• use only as directed • avoid contact with eyes or mucus membranes • do not bandage tightly or use with a heating pad • do not apply to wounds or damaged skin

Stop use and ask doctor if

• condition worsens • redness is present • irritation develops • symptoms persist for more than 7 days or clear up and occur again within a few days

If pregnant or breast-feeding

ask a healthcare professional before use.

Keep out of reach of children.

If swallowed get medical help or contact a Poison Control Center right away.

Directions

Adults and children over 12 years: • apply generously to affected area. • massage into painful area until thoroughly absorbed into skin. • repeat as necessary, but not more than 4 times daily. Children under 12 years: ask a doctor.

Inactive ingredients

Paraffin, White Petrolatum.